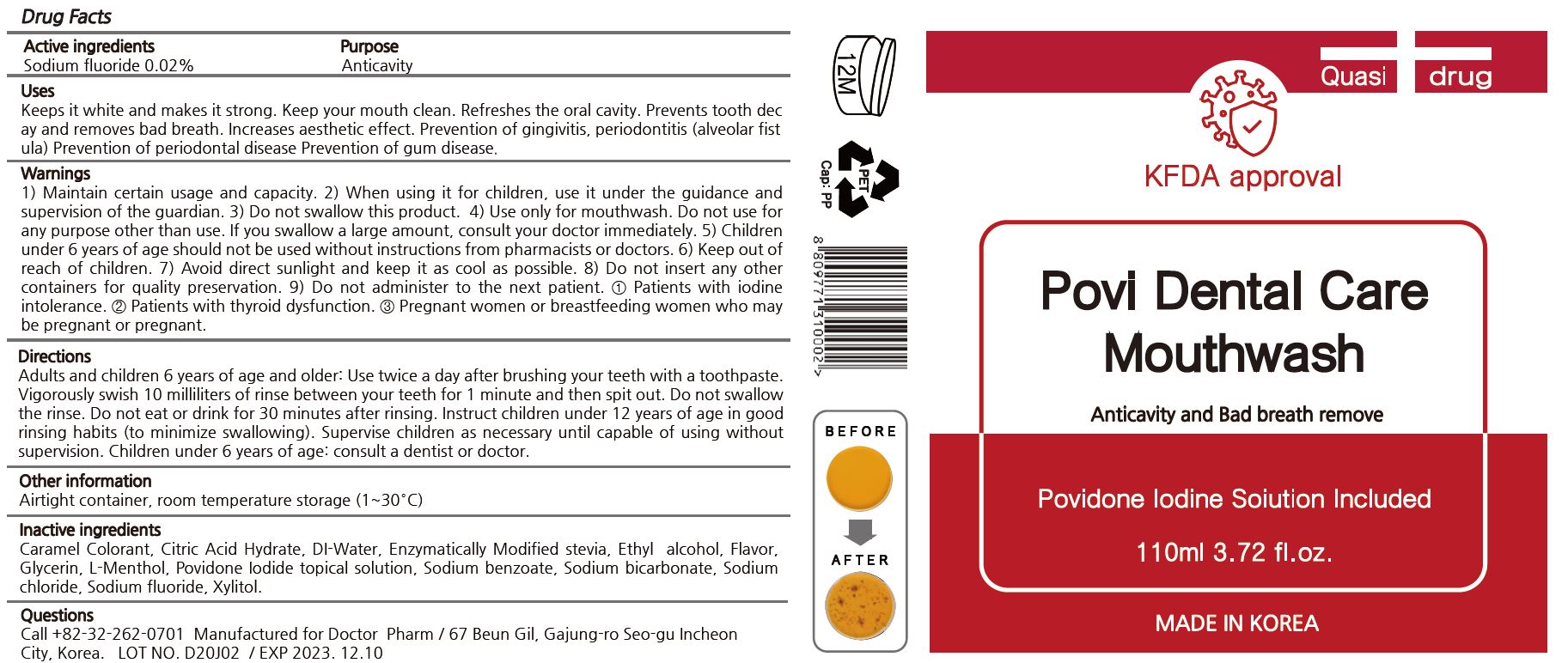 DRUG LABEL: POVI DENTAL CARE
NDC: 81017-0001 | Form: MOUTHWASH
Manufacturer: DOCTOR PHARM
Category: otc | Type: HUMAN OTC DRUG LABEL
Date: 20201106

ACTIVE INGREDIENTS: SODIUM FLUORIDE 0.02 g/100 mL
INACTIVE INGREDIENTS: XYLITOL; CITRIC ACID MONOHYDRATE; CARAMEL; WATER; ALCOHOL; SODIUM CHLORIDE; SODIUM BICARBONATE; GLYCERIN; LEVOMENTHOL; SODIUM BENZOATE; POVIDONE

DOCTOR PHARM - POVI DENTAL CARE MOUTHWASH

ACTIVE INGREDIENT

Sodium Flouride

PURPOSE

Keeps it white and makes it strong.
Keep your mouth clean.
Refreshes the oral cavity.
Prevents tooth decay and removes bad breath.
Increases aesthetic effect.
Prevention of gingivitis, periodontitis (alveolar fistula)
Prevention of periodontal disease
Prevention of gum disease

Keep out of reach of children

INDICATIONS AND USAGE

Adults and children 6 years of age and older: Use twice a day after brushing your teeth with a toothpaste. Vigorously swish 10 milliliters of rinse between your teeth for 1 minute and then spit out. Do not swallow the rinse. Do not eat or drink for 30 minutes after rinsing. Instruct children under 12 years of age in good rinsing habits (to minimize swallowing). Supervise children as necessary until capable of using without supervision. Children under 6 years of age: consult a dentist or doctor.

WARNINGS

1.Maintain certain usage and capacity.
2.When using it for children, use it under the guidance and supervision of the guardian.
3.Do not swallow this product.
4.Use only for mouthwash. Do not use for any purpose other than use. If you swallow a large amount, consult your doctor immediately.
5.Children under 6 years of age should not be used without instructions from pharmacists or doctors.
5.Keep out of reach of children.
6.Avoid direct sunlight and keep it as cool as possible. 8) Do not insert any other containers for quality preservation.
7.Do not administer to the next patient.
1).Patients with iodine intolerance
2).Patients with thyroid dysfunction
3).Pregnant women or breastfeeding women who may be pregnant or pregnant

INACTIVE INGREDIENT

Water, glycerin, ethyl alcohol, xylitol, sodium bicarbonate, flavor, citric acid hydrate, enzymatically modified stevia, sodium benzoate, sodium chloride, caramel color, povidone iodide topical solution, l-menthol

DOSAGE AND ADMINISTRATION

For dental use only